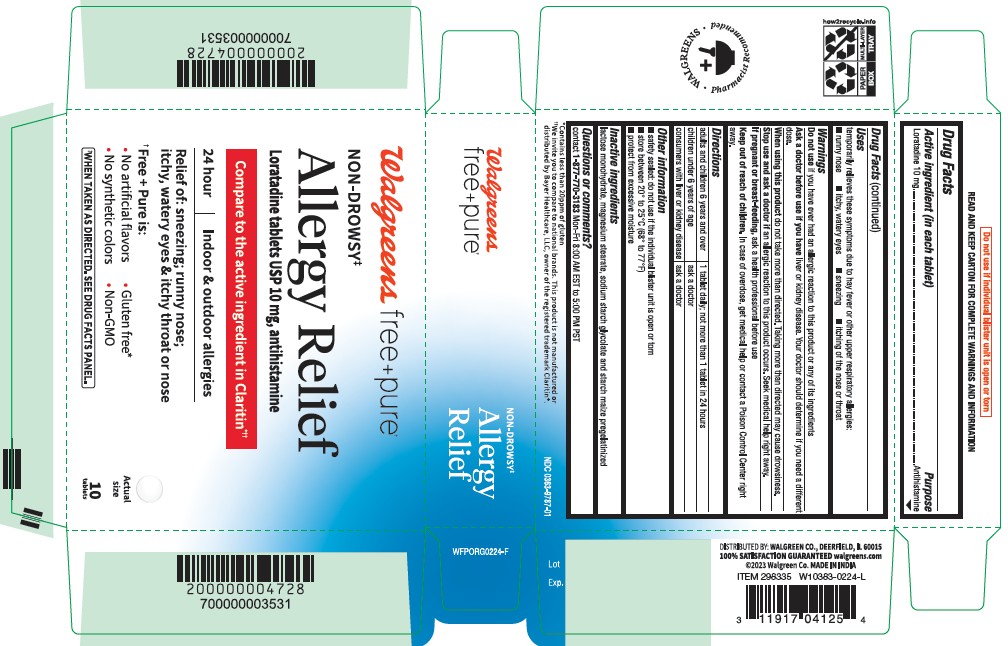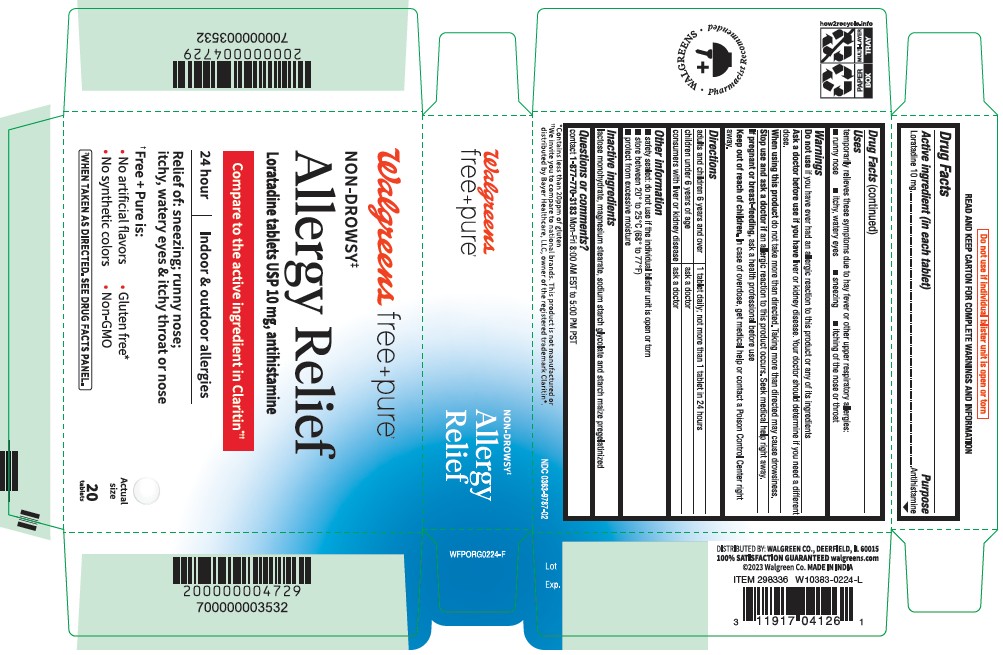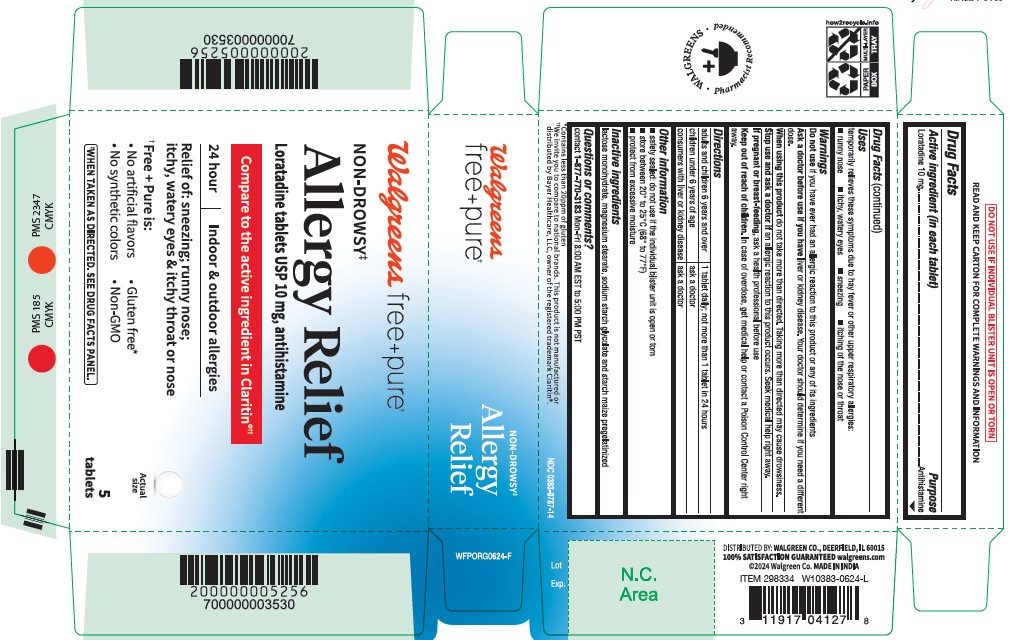 DRUG LABEL: Loratadine
NDC: 0363-9787 | Form: TABLET
Manufacturer: Walgreens
Category: otc | Type: HUMAN OTC DRUG LABEL
Date: 20251219

ACTIVE INGREDIENTS: LORATADINE 10 mg/1 1
INACTIVE INGREDIENTS: SODIUM STARCH GLYCOLATE TYPE A POTATO; STARCH, CORN; MAGNESIUM STEARATE; LACTOSE MONOHYDRATE

Loratadine Tablets USP, 10mg
Antihistamine
Indoor & Outdoor Allergies
Non-Drowsy
24HR
Relief of:
■ Sneezing
■ Runny Nose
■ Itchy, Watery Eyes
■ Itchy Throat or Nose

Active ingredient (in each tablet)

Loratadine 10 mg

Purpose

Antihistamine

Uses

temporarily relieves these symptoms due to hay fever or other upper respiratory allergies:
■ runny nose ■ itchy, watery eyes
■ sneezing ■ itching of the nose or throat

Warnings

Do not use if you have ever had an allergic reaction to this product or any of its ingredients.

Ask a doctor before use if you have

liver or kidney disease. Your doctor should determine if you need a different dose.

When using this product

do not take more than directed. Taking more than directed may cause drowsiness.

Stop use and ask a doctor if

an allergic reaction to this product occurs. Seek medical help right away.

If pregnant or breast-feeding

ask a health professional before use.

Keep out of reach of children

In case of overdose, get medical help or contact a Poison Control Center right away.

Directions

adults and children 1 tablet daily; not more than 1 tablet in 24 hours
6 years and over

children under ask a doctor
6 years of age

consumers with liver ask a doctor
or kidney disease

Other information

■ safety sealed: do not use if the individual blister unit if open or torn
■ store between 20° to 25° C (68° to 77°F)
■ protect from excessive moisture

Inactive ingredients

Lactose monohydrate, magnesium stearate, sodium starch glycolate and starch maize pregelatinized

Questions or comments?

Contact 1-877-770-3183 Mon-Fri 9:00 AM to 4:30 PM EST